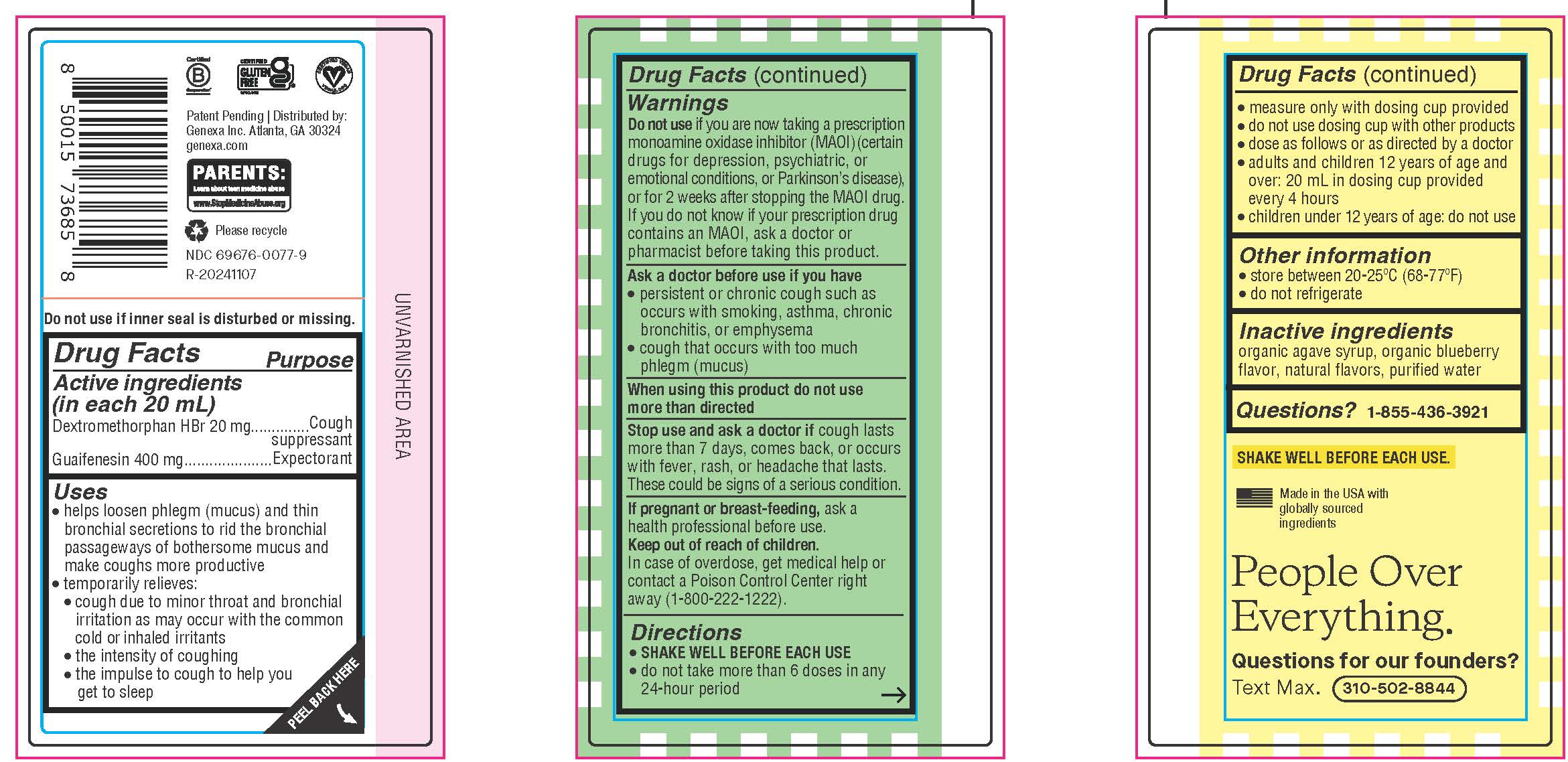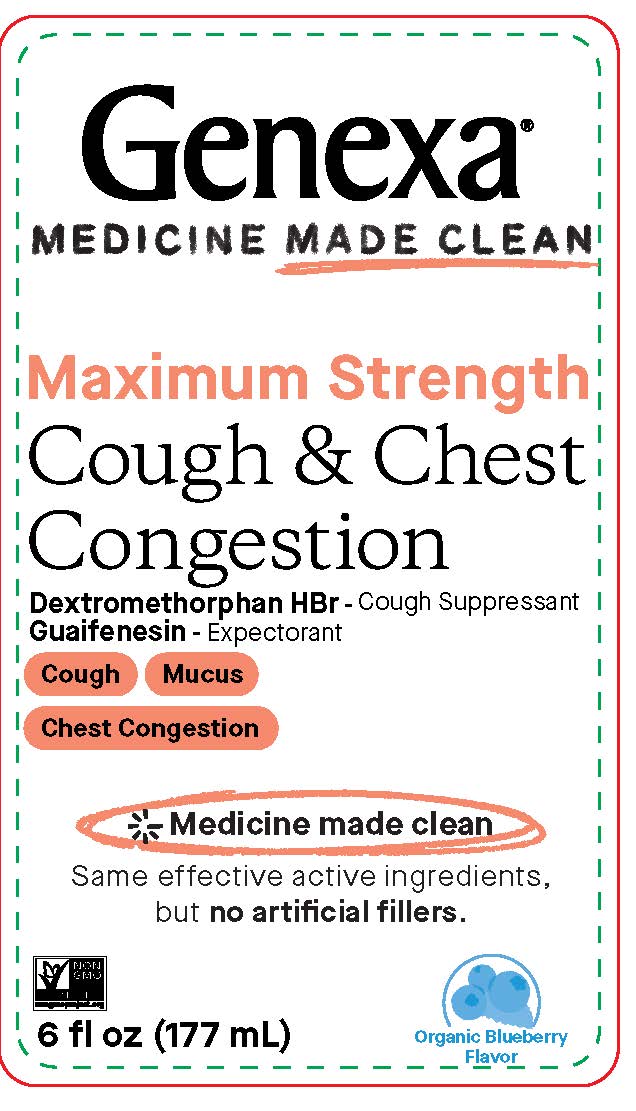 DRUG LABEL: Cough and Chest Congestion Maximum Strength
NDC: 69676-0077 | Form: SUSPENSION
Manufacturer: Genexa Inc.
Category: otc | Type: HUMAN OTC DRUG LABEL
Date: 20250624

ACTIVE INGREDIENTS: GUAIFENESIN 400 mg/20 mL; DEXTROMETHORPHAN HYDROBROMIDE 20 mg/20 mL
INACTIVE INGREDIENTS: AGAVE TEQUILANA JUICE; WATER; BLUEBERRY

Cough and Chest Congestion Maximum Strength

Patent Pending | Distributed by:

Genexa Inc. Atlanta, GA 30324

genexa.com

NDC 69676-0077-9

Do not use if inner seal is disturbed or missing.

Drug Facts

Active ingredients

(in each 20 mL)

Dextromethorphan HBr 20 mg

Guaifenesin 400 mg

Purpose

Cough suppressant

Expectorant

Uses

- helps loosen phlegm (mucus) and thin bronchial secretions to rid the bronchial passageways of bothersome mucus and make coughs more productive
- temporarily relieves:

• cough due to minor throat and bronchial irritation as may occur with the common cold or inhaled irritants

• the intensity of coughing

• the impulse to cough to help you get to sleep

Warnings

Do not use if you are now taking a prescription monoamine oxidase inhibitor (MAOI) (certain drugs for depression, psychiatric, or emotional conditions, or Parkinson’s disease), or for 2 weeks after stopping the MAOI drug. If you do not know if your prescription drug contains an MAOI, ask a doctor or pharmacist before taking this product.

Ask a doctor before use if you have

- persistent or chronic cough such as occurs with smoking, asthma, chronic bronchitis, or emphysema
- cough that occurs with too much phlegm (mucus)

When using this product do not use more than directed

Stop use and ask a doctor if cough lasts more than 7 days, comes back, or occurs with fever, rash or headache that lasts. These could be signs of a serious condition.

PREGNANCY

If pregnant or breast-feeding, ask a health professional before use.

Keep out of reach of children. In case of overdose, get medical help or contact a Poison Control Center right away (1-800-222-1222).

Directions

SHAKE WELL BEFORE EACH USE

- do not take more than 6 doses in any 24-hour period
- measure only with dosing cup provided
- do not use dosing cup with other products
- dose as follows or as directed by a doctor
- adults and children 12 years of age and over: 20 mL in dosing cup provided every 4 hours
- children under 12 years of age: do not use

Other information

- store between 20-25°C (68-77°F)
- do not refrigerate

Inactive ingredients

organic agave syrup, organic blueberry flavor, natural flavors, purified water

Questions?

1-855-436-3921

SHAKE WELL BEFORE EACH USE.

Made in the USA with globally sourced ingredients

Directions

SHAKE WELL BEFORE EACH USE

- do not take more than 6 doses in any 24-hour period
- measure only with dosing cup provided
- do not use dosing cup with other products
- dose as follows or as directed by a doctor
- adults and children 12 years of age and over: 20 mL in dosing cup provided every 4 hours
- children under 12 years of age: do not use

PACKAGE LABEL

Genexa®

MEDICINE MADE CLEAN
Maximum Strength

Cough & Chest Congestion

Dextromethorphan HBr - Cough Suppressant

Guaifenesin - Expectorant

Cough

Mucus

Chest Congestion

Medicine made clean

Same effective active ingredients, but no artificial fillers.

Organic Blueberry Flavor

6 fl oz (177 mL)